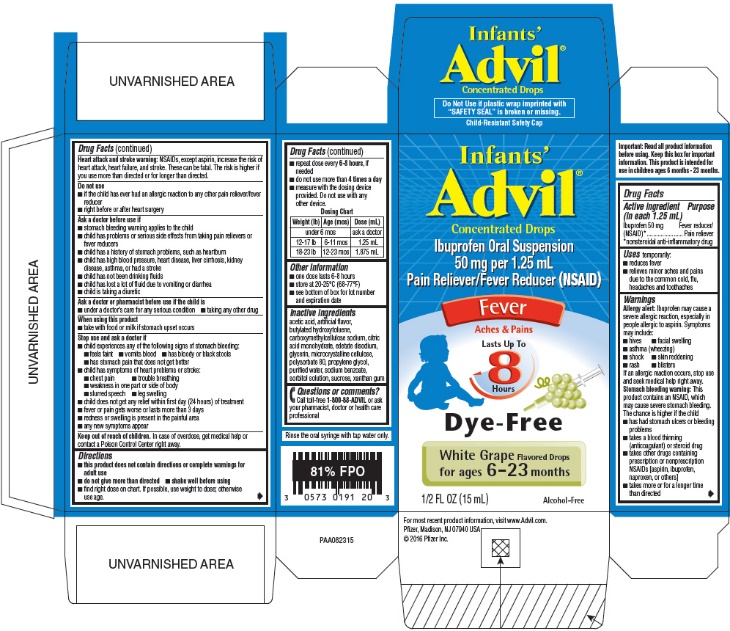 DRUG LABEL: INFANTS ADVIL
NDC: 0573-0191 | Form: SUSPENSION/ DROPS
Manufacturer: Haleon US Holdings LLC
Category: otc | Type: HUMAN OTC DRUG LABEL
Date: 20241126

ACTIVE INGREDIENTS: IBUPROFEN 50 mg/1.25 mL
INACTIVE INGREDIENTS: ACETIC ACID; BUTYLATED HYDROXYTOLUENE; CARBOXYMETHYLCELLULOSE SODIUM, UNSPECIFIED; CITRIC ACID MONOHYDRATE; EDETATE DISODIUM; GLYCERIN; MICROCRYSTALLINE CELLULOSE; POLYSORBATE 80; PROPYLENE GLYCOL; WATER; SODIUM BENZOATE; SORBITOL; SUCROSE; XANTHAN GUM

Drug Facts

Active ingredient (in each 1.25 mL)

Ibuprofen 50 mg (NSAID) [nonsteroidal anti-inflammatory drug]

Purpose

Fever reducer/Pain reliever

Uses

temporarily:

- reduces fever
- relieves minor aches and pains due to the common cold, flu, headaches and toothaches

Warnings

Allergy alert

Ibuprofen may cause a severe allergic reaction, especially in people allergic to aspirin. Symptoms may include:

- hives
- facial swelling
- asthma (wheezing)
- shock
- skin reddening
- rash
- blisters

If an allergic reaction occurs, stop use and seek medical help right away.

Stomach bleeding warning

This product contains an NSAID, which may cause severe stomach bleeding. The chance is higher if the child

- has had stomach ulcers or bleeding problems
- takes a blood thinning (anticoagulant) or steroid drug
- takes other drugs containing prescription or nonprescription NSAIDs [aspirin, ibuprofen, naproxen, or others]
- takes more or for a longer time than directed

Heart attack and stroke warning

NSAIDs, except aspirin, increase the risk of heart attack, heart failure, and stroke. These can be fatal. The risk is higher if you use more than directed or for longer than directed.

Do not use

- if the child has ever had an allergic reaction to any other pain reliever/fever reducer
- right before or after heart surgery

Ask a doctor before use if

- stomach bleeding warning applies to the child
- child has problems or serious side effects from taking pain relievers or fever reducers
- child has a history of stomach problems, such as heartburn
- child has high blood pressure, heart disease, liver cirrhosis, kidney disease, asthma, or had a stroke
- child has not been drinking fluids
- child has lost a lot of fluid due to vomiting or diarrhea
- child is taking a diuretic

Ask a doctor or pharmacist before use if the child is

- under a doctor's care for any serious condition
- taking any other drug

When using this product

- take with food or milk if stomach upset occurs

Stop use and ask a doctor if

- child experiences any of the following signs of stomach bleeding:
  - feels faint
  - vomits blood
  - has bloody or black stools
  - has stomach pain that does not get better
- child has symptoms of heart problems or stroke:
  - chest pain
  - trouble breathing
  - weakness in one part or side of the body
  - slurred speech
  - leg swelling
- child does not get any relief within first day (24 hours) of treatment
- fever or pain gets worse or lasts more than 3 days
- redness or swelling is present in the painful area
- any new symptoms appear

Keep out of reach of children. In case of overdose, get medical help or contact a Poison Control Center right away.

Directions

- this product does not contain directions or complete warnings for adult use
- do not give more than directed
- shake well before using
- find right dose on chart below. If possible, use weight to dose; otherwise use age.
- repeat dose every 6-8 hours, if needed
- do not use more than 4 times a day
- measure with the dosing device provided. Do not use with any other device.

Dosing Chart
Weight (lb) | Age (mos) | Dose (mL)
under 6 mos |  | ask a doctor
12-17 lb | 6-11 mos | 1.25 mL
18-23 lb | 12-23 mos | 1.875 mL

Other Information

- one dose lasts 6-8 hours
- store at 20-25°C (68-77°F)
- see bottom of box for lot number and expiration date

Inactive ingredients

acetic acid, artificial flavor, butylated hydroxytoluene, carboxymethylcellulose sodium, citric acid monohydrate, edetate disodium, glycerin, microcrystalline cellulose, polysorbate 80, propylene glycol, purified water, sodium benzoate, sorbitol solution, sucrose, xanthan gum

Questions or comments?

Call toll-free 1-800-88-ADVIL or ask your pharmacist, doctor or health care professional

For most recent product information, visit www.Advil.com.

PRINCIPAL DISPLAY PANEL

Infants'
Advil®
Concentrated Drops

Ibuprofen Oral Suspension
50 mg per 1.25 mL
Pain Reliever/Fever Reducer (NSAID)

Fever

Aches & Pains

Lasts Up To
8
Hours

Dye-Free

White Grape Flavored Drops
for ages 6–23 months

1/2 FL OZ (15 mL)
Alcohol-Free